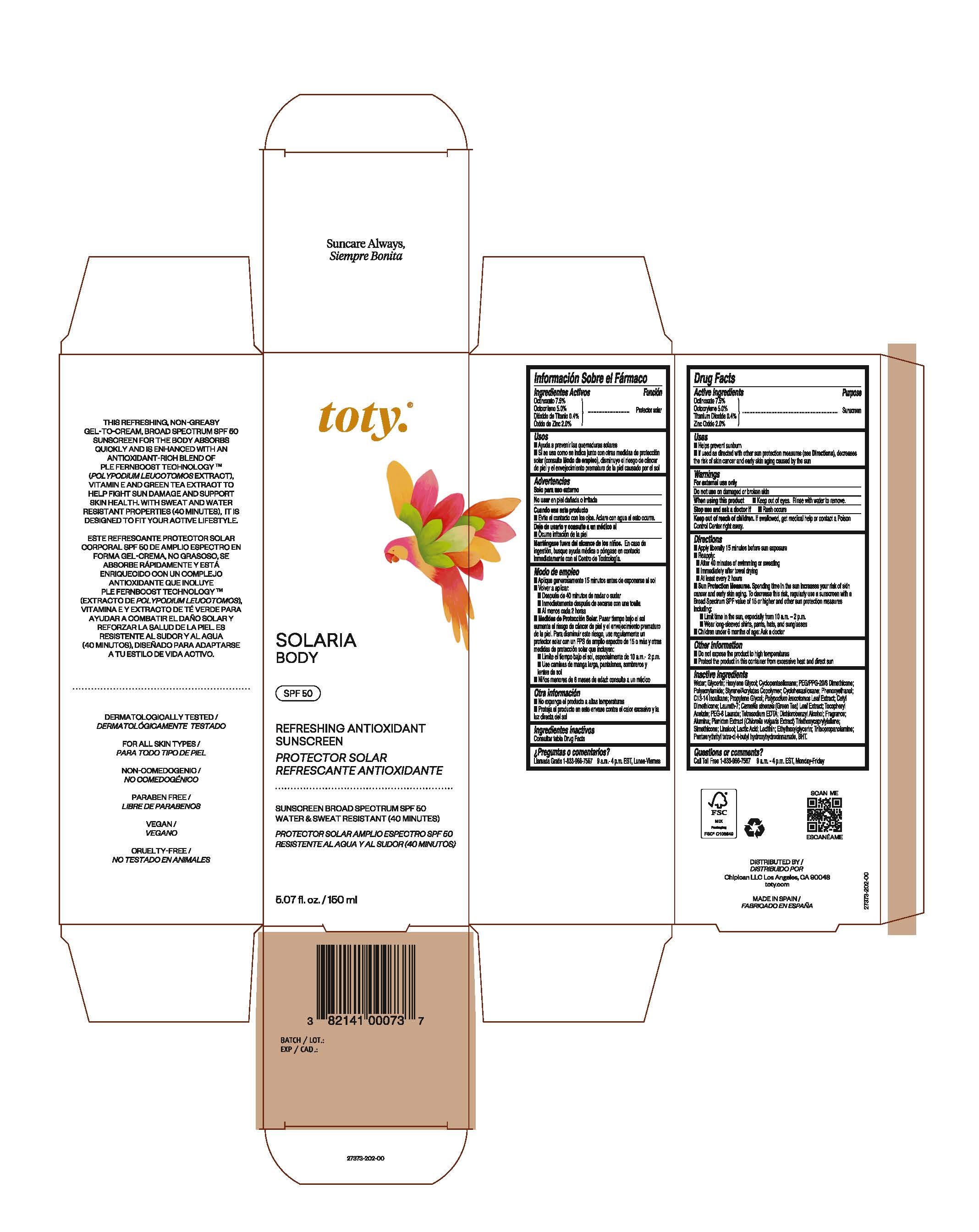 DRUG LABEL: toty Solaria Body
NDC: 82141-7373 | Form: CREAM
Manufacturer: CHIPICAN LLC
Category: otc | Type: HUMAN OTC DRUG LABEL
Date: 20240604

ACTIVE INGREDIENTS: OCTOCRYLENE 5 g/100 g; OCTINOXATE 7.5 g/100 g; ZINC OXIDE 2 g/100 g; TITANIUM DIOXIDE 0.4 g/100 g
INACTIVE INGREDIENTS: PENTAERYTHRITOL TETRAKIS(3-(3,5-DI-TERT-BUTYL-4-HYDROXYPHENYL)PROPIONATE); LACTIC ACID; ETHYLHEXYLGLYCERIN; PHENOXYETHANOL; LAURETH-7; TRIETHOXYCAPRYLYLSILANE; BUTYL METHACRYLATE/METHYL METHACRYLATE/METHACRYLIC ACID/STYRENE CROSSPOLYMER; TRIISOPROPANOLAMINE; GREEN TEA LEAF; EDETATE SODIUM; BUTYLATED HYDROXYTOLUENE; PROPYLENE GLYCOL; PHLEBODIUM AUREUM LEAF; DICHLOROBENZYL ALCOHOL; .ALPHA.-TOCOPHEROL ACETATE; CHLORELLA VULGARIS; POLYACRYLAMIDE (CROSSLINKED; 0.01-0.2 MOLE PERCENT BISACRYLAMIDE); CETYL DIMETHICONE 150; SILICON DIOXIDE; LINALOOL, (+/-)-; ALUMINUM OXIDE; GLYCERIN; PEG-8 LAURATE; WATER; HEXYLENE GLYCOL; CYCLOMETHICONE 5; PEG/PPG-20/6 DIMETHICONE; CYCLOMETHICONE 6; C13-14 ISOPARAFFIN; SOYBEAN LECITHIN

toty Solaria Body

Active Ingredients

Octinoxate 7.5%

Octocrylene 5.0%

Titanium Dioxide 0.4%

Zinc Oxide 2.0%

Purpose

Sunscreen

Uses

Helps prevent sunburn

If used as directed with other sun protection measures (see Directions), decreases the risk of skin cancer and early skin aging caused by the sun

Warnings

For external use only

Do not use on damaged or broken skin

When using this product Keep out of eyes. Rinse with water to remove.

Stop use and ask a doctor if Rash occurs

Keep out of reach of children. If swallowed, get medical help or contact a Poison Control Center right away.

Directions

Apply liberally 15 minutes before sun exposure

Reapply:

After 40 minutes of swimming or sweating

Immediately after towel drying

At least every 2 hours

Sun protection Measures. Spending time in the sun increases your risk of skin cancewr and early skin aging. To decrease this risk, regularly use a sunscreen with a Broad Spectrum SPF value of 15 or higher and other sun protection measures including:

Limit time in the sun, especially from 10 a.m. - 2 p.m.

Wear long-sleeved shirts, pants, hats, and sunglasses

Children under 6 months of age: Ask a doctor

Other information

Do not expose the product to high temperatures

Protect the product in this container from excessive heat and direct sun.

Inactive Ingredients

Water; Glycerin: Hexylene Glycol; Cyclopentasiloxane; PEG/PPG-20/6 Dimethicone;

Polycrylamide; Styrene/Acrylates Copolymer; Cyclohexasiloxane; Phenoxyethanol;

C13-14 Isoalkane; Propylene Glycol; Polypodium leucotomos Leaf Extract; Cetyl

Dimethicone; Laureth-7; Camellia sinensis (Green tea) Leaf Extract; Tocopheryl

Acetate; PEG-8 Laurate; Tetrasodium EDTA; Dicholorobenzyl Alcohol; Fragrance;

Alumina; Plankton Extract (Chlorella vulgaris Extract); Triethoxycaprylylsilane;

Simethicone; Linalool; Lactic Acid; Lecithin; Ethylhexylglycerin, Triisopropanolamine;

Pentaerythrityl tetra-di-t-butyl hydroxyhydrocinnamate, BHT.

Package Label. Principal Display Panel

toty.®

SOLARIA

BODY

SPF 50

REFRESHING ANTIOXIDANT

SUNSCREEN

PROTECTOR SOLAR

REFRESCANTE ANTIOXIDANTE

SUNSCREEN BROAD SPECTRUM SPF 50

WATER & SWEAT RESISTANT (40 MINUTES)

PROTECTOR SOLAR AMPLIO ESPECTRO SPF 50

RESISTENTE AL AGUA Y AL SUDOR (40 MINUTOS)

5.07 fl. oz./ 150 ml